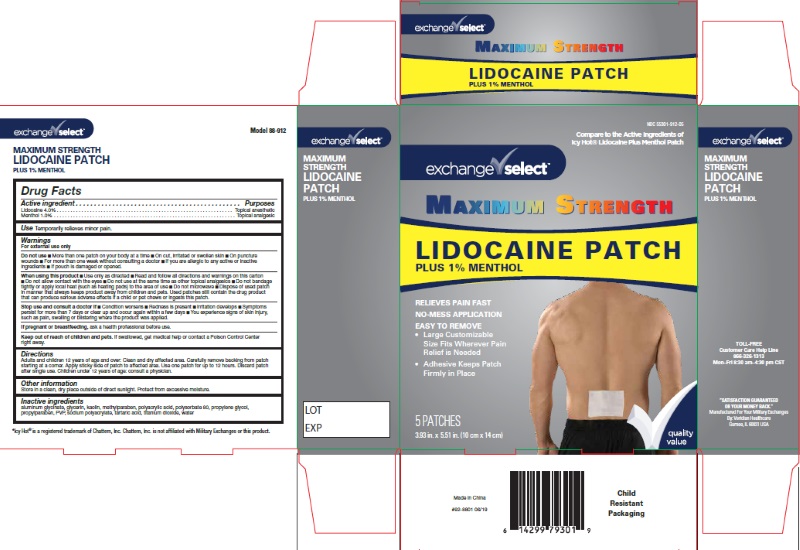 DRUG LABEL: MAXIMUM STRENGTH Lidocaine Plus Menthol
NDC: 55301-912 | Form: PATCH
Manufacturer: ARMY AND AIR FORCE EXCHANGE SERVICE
Category: otc | Type: HUMAN OTC DRUG LABEL
Date: 20251230

ACTIVE INGREDIENTS: LIDOCAINE 4 g/100 g; MENTHOL, UNSPECIFIED FORM 1 g/100 g
INACTIVE INGREDIENTS: DIHYDROXYALUMINUM AMINOACETATE ANHYDROUS; GLYCERIN; KAOLIN; METHYLPARABEN; POLYACRYLIC ACID (250000 MW); POLYSORBATE 80; PROPYLENE GLYCOL 1-(2-METHYLBUTYRATE); PROPYLPARABEN; POVIDONE, UNSPECIFIED; SODIUM POLYACRYLATE (2500000 MW); TARTARIC ACID; TITANIUM DIOXIDE; WATER

MAXIMUM STRENGTH Lidocaine Plus Menthol

ACTIVE INGREDIENT

Lidocaine 4% Topical Anesthetic

Menthol 1% Topical Anesthetic

PURPOSE

Topical Anesthetic

USES

Temporary relief of minor pain

WARNINGS

- For External use only. Use only as directed.

- Keep out of reach of children. If swallowed, get medical help or contact a Poison Control Center right away.

DO NOT USE

■ More than one patch on your body at a time

■ On cut, irritated or swollen skin

■ On puncture wounds

■ For more than one week without consulting a doctor

■ If you are allergic to any active or inactive ingredients

■ If pouch is damaged or opened.

If pregnant or breast feeding

- Contact a physician prior to use.

WHEN USING:

■ Use only as directed

■ Read and follow all directions and warnings on this carton

■ Do not allow contact with the eyes

■ Do not use at the same time as other topical analgesics

■ Do not bandage tightly or apply local heat (such as heating pads) to the area of use

■ Do not microwave

■ Dispose of used patch in manner that always keeps product away from children and pets. Used patches still contain
the drug product that can produce serious adverse effects if a child or pet chews or ingests this patch.

Stop use and consult a doctor if

■ Condition worsens

■ Redness is present

■ Irritation develops

■ Symptoms persist for more than 7 days or clear up and occur again within a few days

■ You experience signs of skin injury, such as pain, swelling or blistering where the product was applied.

DIRECTIONS Adults and children 12 years of age and over:

Clean and dry affected area. Carefully remove backing from patch starting at a corner. Apply sticky side
of patch to affected area. Use one patch for up to 12 hours. Discard after single use.
Children under 12 years of age: consult a physician.

INACTIVE INGREDIENTS

aluminum glycinate, glycerin, kaolin, methylparaben, polyacrylic acid, polysorbate 80, propylene glycol,
propylparaben, PVP, sodium polyacrylate, tartaric acid, titanium dioxide, water

STORAGE AND HANDLING

Store in a clean, dry place outside of direct sunlight. Protect from excessive moisture.

Lidocaine + Menthol Patch

TOLL-FREE

Customer Care Help Line
866-326-1313
Mon–Fri 8:30 am–4:30 pm CST

Manufactured for Your Military Exchangers By
Veridian Healthcare
Gurnee, IL 60031